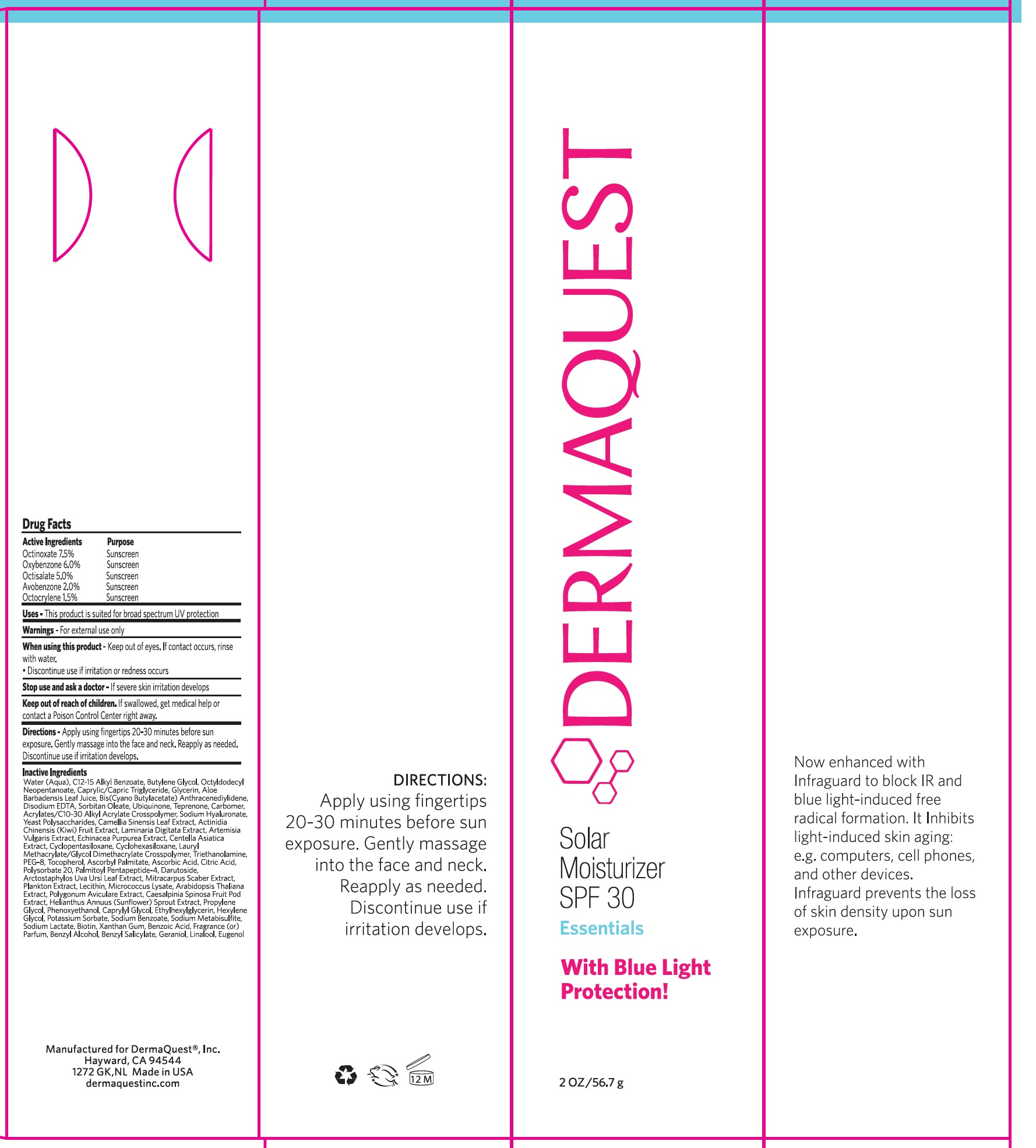 DRUG LABEL: Solar Moisturizer SPF 30
NDC: 62742-4078 | Form: CREAM
Manufacturer: Allure Labs, LLC
Category: otc | Type: HUMAN OTC DRUG LABEL
Date: 20241205

ACTIVE INGREDIENTS: OCTISALATE 5 mg/1 g; OCTINOXATE 7.5 mg/1 g; OXYBENZONE 6 mg/1 g; AVOBENZONE 2 mg/1 g; OCTOCRYLENE 1.5 mg/1 g
INACTIVE INGREDIENTS: BUTYL CYANOACETATE; YEAST; ECHINACEA PURPUREA; LAURYL METHACRYLATE/GLYCOL DIMETHACRYLATE CROSSPOLYMER; BIOTIN; WATER; GREEN TEA LEAF; CENTELLA ASIATICA; CYCLOMETHICONE 5; CYCLOMETHICONE 6; TOCOPHEROL; ASCORBIC ACID; CITRIC ACID MONOHYDRATE; PALMITOYL PENTAPEPTIDE-4; DARUTOSIDE; SODIUM BENZOATE; SODIUM METABISULFITE; SODIUM LACTATE; XANTHAN GUM; BENZOIC ACID; BENZYL ALCOHOL; GERANIOL; POLYETHYLENE GLYCOL 400; EDETATE DISODIUM ANHYDROUS; SORBITAN MONOOLEATE; UBIDECARENONE; POTASSIUM SORBATE; BENZYL SALICYLATE; LINALOOL, (+/-)-; EUGENOL; BUTYLENE GLYCOL; OCTYLDODECYL NEOPENTANOATE; MEDIUM-CHAIN TRIGLYCERIDES; GLYCERIN; POLYGONUM AVICULARE TOP; TEPRENONE; CARBOMER HOMOPOLYMER, UNSPECIFIED TYPE; CAESALPINIA SPINOSA FRUIT POD; HELIANTHUS ANNUUS SPROUT; LECITHIN, SOYBEAN; MICROCOCCUS LUTEUS; CAPRYLYL GLYCOL; ETHYLHEXYLGLYCERIN; HEXYLENE GLYCOL; LAMINARIA DIGITATA; TROLAMINE; ASCORBYL PALMITATE; POLYSORBATE 20; ARCTOSTAPHYLOS UVA-URSI LEAF; MITRACARPUS HIRTUS WHOLE; ARABIDOPSIS THALIANA WHOLE; PROPYLENE GLYCOL; PHENOXYETHANOL; ALOE VERA LEAF; CARBOMER INTERPOLYMER TYPE A (55000 CPS); HYALURONATE SODIUM; KIWI FRUIT; ARTEMISIA VULGARIS WHOLE; ALKYL (C12-15) BENZOATE

Drug Facts

Active Ingredients:

Octinoxate - 7.5%

Oxybenzone - 6.0%

Octisalate - 5.0%

Avobenzone - 2.0%

Octocrylene - 1.5%

Purpose: Sunscreen

INDICATIONS AND USAGE

Uses - This product is suited for broad spectrum UV Protection.

Warnings - For external use only.

When using this product - Keep out of eyes. If contact occurs, rinse with water.

- Discontinue use if irritation or redness occurs.

Stop use and ask a doctor - If severe skin irritation develops.

Keep out of reach of children.

- If swallowed, get medical help or contact a Poison Control Center right away.

DOSAGE AND ADMINISTRATION

Directions - Apply using fingertips 20-30 minutes before sun exposure. Gentely massage into face and neck. Reapply as needed. Discontinue use if irritation develops.

Inactive Ingredients:

Water (Aqua), C12-15 Alkyl Benzoate, Butylene Glycol, Octyldodecyl Neopentanoate, Caprylic/Capric Triglyceride, Glycerin , Aloe Barbadensis Leaf Juice , Bis(Cyano Butylacetate) Anthracenediylidene, Disodium EDTA, Sorbitan Oleate, Ubiquinone, Teprenone, Carbomer, Acrylates/C10-30 Alkyl Acrylate Crosspolymer, Sodium Hyaluronate, Yeast Polysaccharides, Camellia Sinensis Leaf Extract, Actinidia Chinensis (Kiwi) Fruit Extract, Laminaria Digitata Extract, Artemisia Vulgaris Extract, Echinacea Purpurea Extract, Centella Asiatica Extract , Cyclopentasiloxane, Cyclohexasiloxane, Lauryl Methacrylate/Glycol Dimethacrylate Crosspolymer, Triethanolamine , PEG-8, Tocopherol , Ascorbyl Palmitate , Ascorbic Acid , Citric Acid, Polysorbate 20, Palmitoyl Pentapeptide-4, Darutoside, Arctostaphylos Uva Ursi Leaf Extract , Mitracarpus Scaber Extract, Plankton Extract , Lecithin , Micrococcus Lysate, Arabidopsis Thaliana Extract , Polygonum Aviculare Extract, Caesalpinia Spinosa Fruit Pod Extract, Helianthus Annuus (Sunflower) Sprout Extract, Propylene Glycol, Phenoxyethanol, Caprylyl Glycol , Ethylhexylglycerin , Hexylene Glycol, Potassium Sorbate, Sodium Benzoate , Sodium Metabisulfite, Sodium Lactate, Biotin, Xanthan Gum, Benzoic Acid, Fragrance (or) Parfum, Benzyl Alcohol, Benzyl Salicylate, Geraniol, Linalool, Eugenol

PACKAGE LABEL

Manufactured for DermaQuest®, Inc.

Hayward, CA 94544

1272 GK, NL Made in USA

dermaquestinc.com